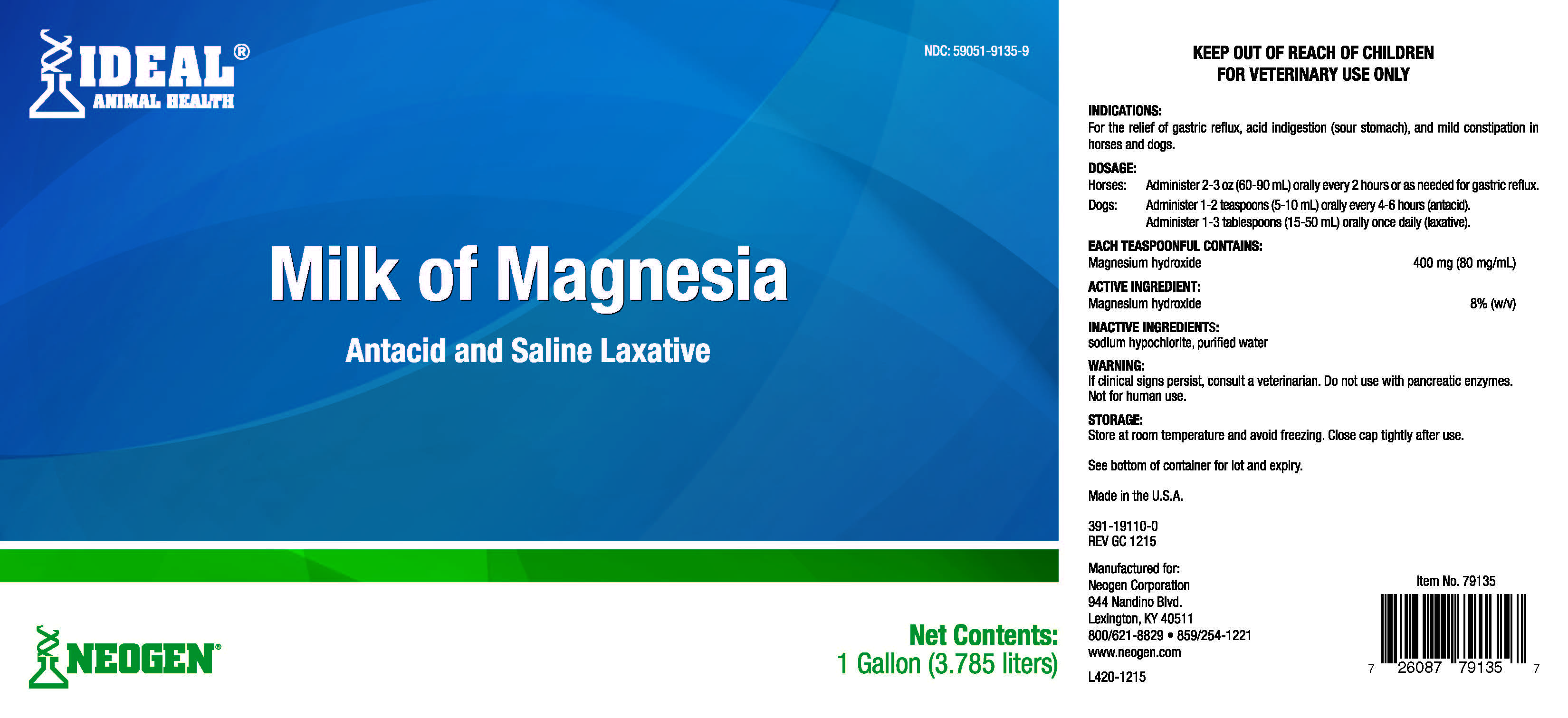 DRUG LABEL: Milk of Magnesia
NDC: 59051-9135 | Form: LIQUID
Manufacturer: Neogen Corporation-Mercer Rd
Category: animal | Type: OTC ANIMAL DRUG LABEL
Date: 20240523

ACTIVE INGREDIENTS: MAGNESIUM HYDROXIDE 80 mg/1 mL
INACTIVE INGREDIENTS: SODIUM HYPOCHLORITE; WATER

Milk Of Magnesia
ANTACID-LAXATIVE

INDICATIONS:

For the relief of gastric reflux, acid indigestion (sour stomach), and mild constipation in horses and dogs.

DOSAGE:

Horses: Adminsiter 2-3 oz (60-90 mL) orally every 2 hours or as needed for gastric reflux.

Dogs: Administer 1-2 teaspoons (5-10 mL) orally every 4-6 hours (antacid).

Administer 1-3 teaspoons (15-50 mL) orally once daily (laxative).

EACH TEASPOON CONTAINS:

Magnesium hydroxide 400 mg (80 mg/mL)

ACTIVE INGREDIENTS:

Magnesium hydroxide 8% (w/v)

INACTIVE INGREDIENTS:

Sodium hypochlorite, purified water

WARNING:

KEEP OUT OF REACH OF CHILDREN

NOT FOR HUMAN USE

FOR VETERINARY USE ONLY

If clinical signs persist, consult a veterinarian. Do not use with pancreatic enzymes. Not for human use.

See bottom of container for lot and expiry.

Made in the U.S.A.

391-19110-0

REV GC 1215

Manufactured for:

Neogen Corporation

944 Nandino Blvd

Lexington, KY 40511

800/621-8829 • 859/254-1221

www.neogen.com

Item No. 79193

L420-1215

Storage:

Store at room temperature and avoid freezing. Close cap tightly after use.

PRINCIPAL DISPLAY PANEL - 1 Gallon Jug

IDEAL Animal Health

NDC: 59051-9135-9

Milk of Magnesia

Antacid and Saline Laxative

Net Contents:

1 Gallon (3.785 liter)